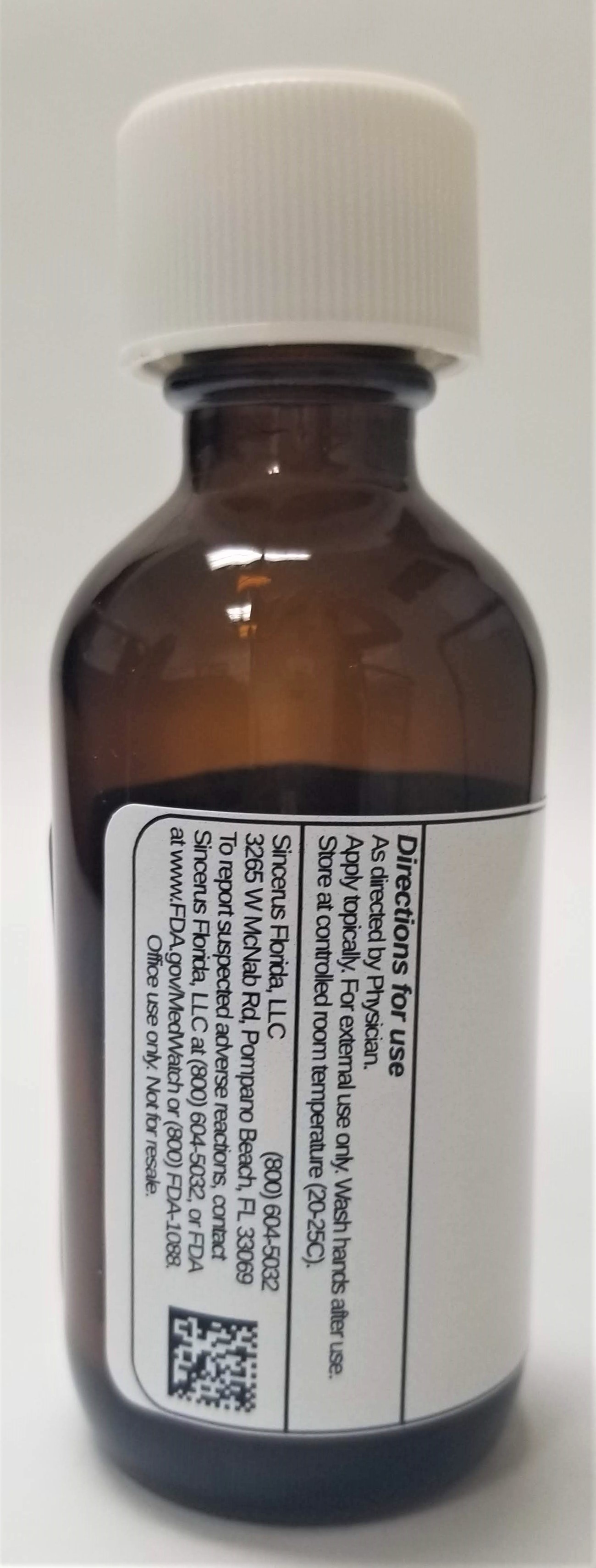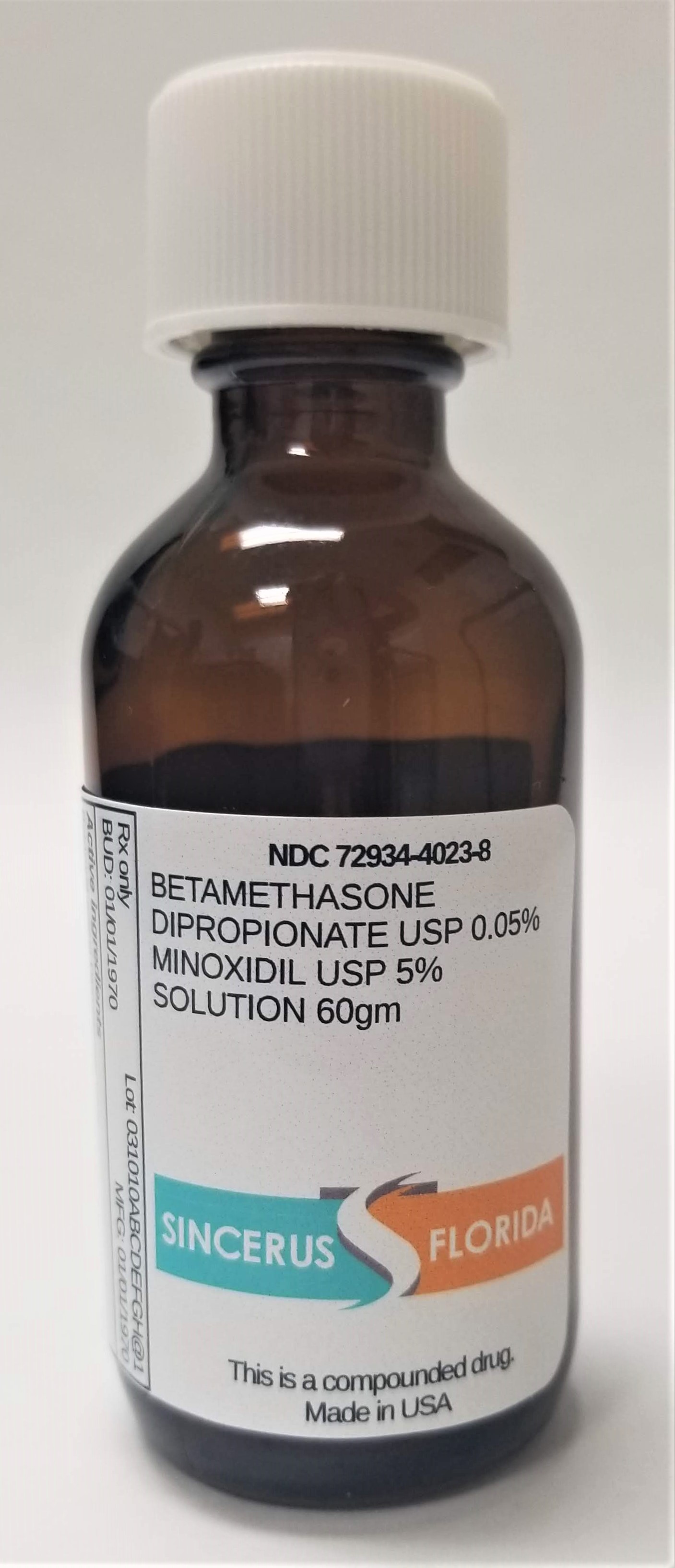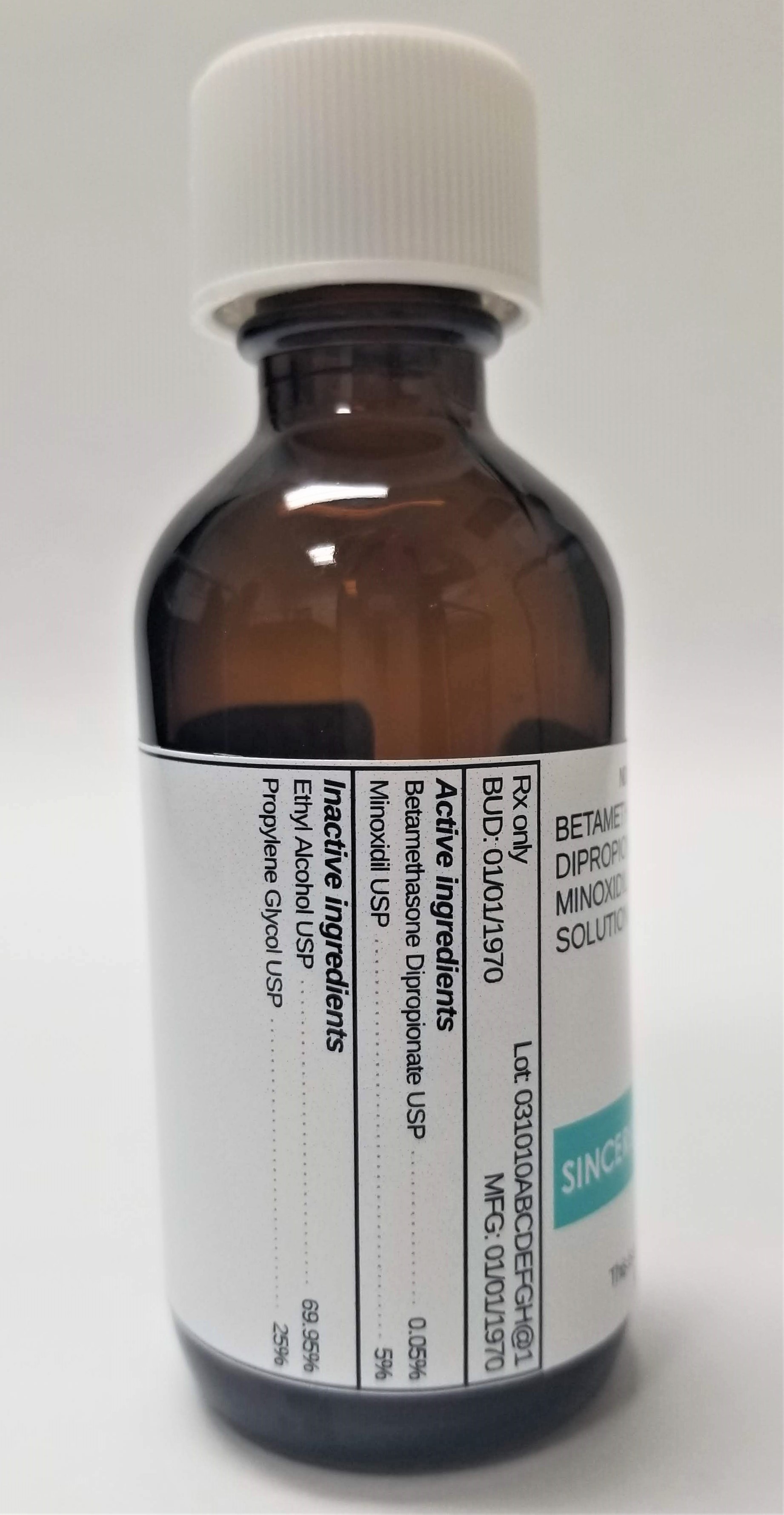 DRUG LABEL: BETAMETHASONE DIPROPIONATE 0.05% / MINOXIDIL 5%
NDC: 72934-4023 | Form: SOLUTION
Manufacturer: Sincerus Florida, LLC
Category: prescription | Type: HUMAN PRESCRIPTION DRUG LABEL
Date: 20190424

ACTIVE INGREDIENTS: MINOXIDIL 5 g/100 g; BETAMETHASONE DIPROPIONATE 0.05 g/100 g

BETAMETHASONE DIPROPIONATE 0.05% / MINOXIDIL 5%